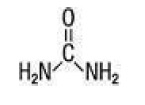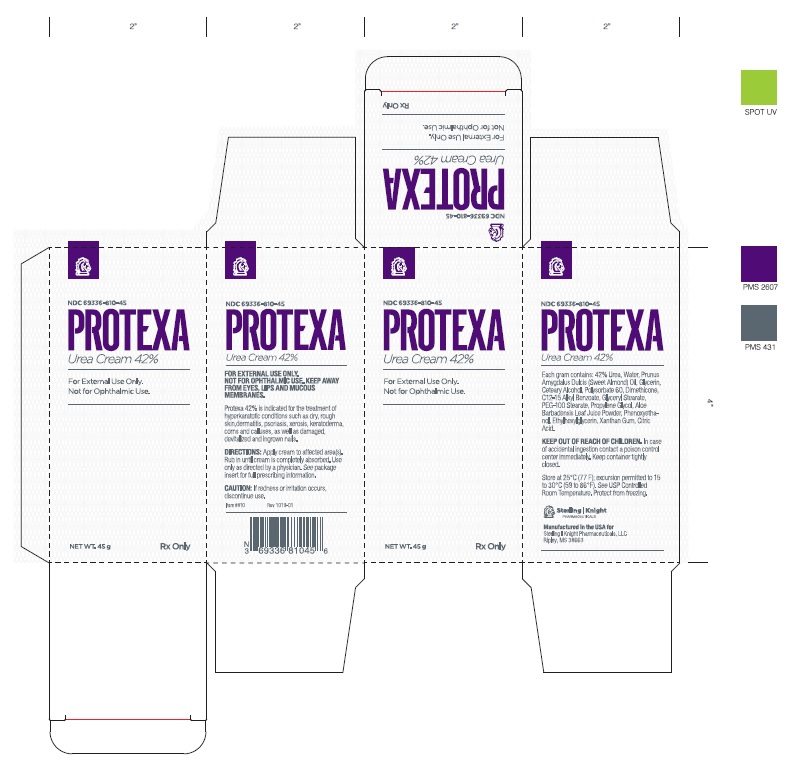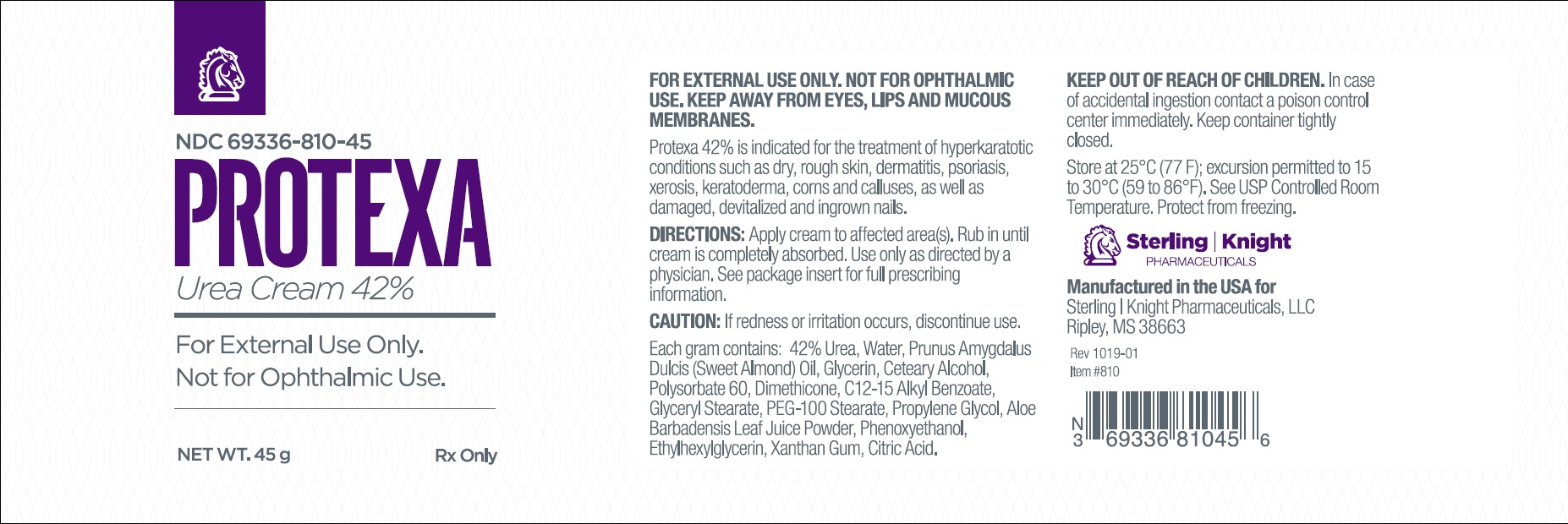 DRUG LABEL: Not Applicable
NDC: 69336-810 | Form: CREAM
Manufacturer: Sterling-Knight Pharmaceuticals, LLC
Category: prescription | Type: HUMAN PRESCRIPTION DRUG LABEL
Date: 20200218

ACTIVE INGREDIENTS: Urea 42 mg/1 g
INACTIVE INGREDIENTS: Water; ALMOND OIL; GLYCERIN; Polysorbate 60; Dimethicone; ALKYL (C12-15) BENZOATE; GLYCERYL STEARATE SE; PEG-100 Stearate; Propylene Glycol; Aloe; Phenoxyethanol; Ethylhexylglycerin; Xanthan Gum; CITRIC ACID ACETATE

Protexa
Urea 42% CreamRx Only FOR EXTERNAL USE ONLY. NOT FOR OPHTHALMIC USE.

DESCRIPTION:

Protexa Cream (42% Urea) is a keratolytic emollient which is gentle, yet potent, tissue softener for nails and/or skin. Each gram contains 42% Urea, Water, Prunus Amygdalus Dulcis (Sweet Almond) Oil, Glycerin, Ceteary Alcohol, Polysorbate 60, Dimethicone, C12-15 Alkyl Benzoate, Glyceryl Stearate, PEG-100 Stearate, Propylene Glycol, Aloe Barbadensis Leaf Juice Powder, Phenoxyethanol, Ethylhexylglycerin, Xanthan Gum, Citric Acid. Urea Urea is a diamide of carbonic acid with the following chemical structure:

CLINICAL PHARMACOLOGY:

Urea gently dissolves the intercellular matrix which results in loosening the horny layer of skin and shedding scaly skin at regular intervals, thereby softening hyperkeratotic areas of the skin.
Pharmacokinetics: The mechanism of action of topically applied urea is not yet known.

INDICATIONS AND USAGE:

This product is useful for the treatment of hyperkeratotic conditions such as dry, rough skin, xerosis, ichthyosis, skin cracks and fissures, dermatitis, eczema, psoriasis, keratoses and calluses.

CONTRAINDICATIONS:

This product is contraindicated in persons with known or suspected hypersensitivity to any of the ingredients of the product

WARNINGS:

KEEP OUT OF REACH OF CHILDREN.
PRECAUTIONS: FOR EXTERNAL USE ONLY. NOT FOR OPHTHALMIC USE.
General:
This product is to be used as directed by a physician and should not be used to treat any condition other than that for which it was prescribed. If redness or irritation occurs, discontinue use and consult a physician.

Information for Patients:

Patients should discontinue the use of this product if the condition becomes worse or if a rash develops in the area being treated or elsewhere. Avoid contact with eyes, lips and mucous membranes.
Carcinogenesis, Mutagenesis and Impairment of Fertility: Long-term animal studies for carcinogenic potential have not been performed on this product to date. Studies on reproduction and fertility also have not been performed.

Pregnancy:

Category C.
Animal reproduction studies have not been conducted with this product. It is also not known whether this product can affect reproduction capacity or cause fetal harm when administered to a pregnant woman. This product should be used by a pregnant woman only if clearly needed or when potential benefits outweigh potential hazards to the fetus.

Nursing Mothers:

It is not known whether this drug is excreted in human milk. Because many drugs are excreted in human milk, caution should be exercised when this product is administered to a nursing woman.

ADVERSE REACTIONS:

Transient stinging, burning, itching or irritation may occur and normally disappear upon discontinuing the use of this product.
CALL YOUR DOCTOR ABOUT SIDE EFFECTS.
Call your doctor about side effects. You may report side effects to the FDA at 1-800-FDA-1088.

DOSAGE AND ADMINISTRATION:

Apply to affected area(s) twice per day or as directed by a physician. Rub in until completely absorbed.

HOW SUPPLIED:

Protexa Cream (42% Urea) is available as follows: 45g container, NDC 69336-810-45

KEEP THIS AND ALL MEDICATIONS OUT OF REACH OF CHILDREN.

All prescriptions using this product shall be pursuant to state statutes as applicable. This is not an Orange Book product. This product may be administered only under a physician’s supervision. There are no implied or explicit claims on the therapeutic equivalence.

Store at 20°C to 25°C (68°F to 77°F), excursions permitted between 15°C to 30°C (between 59°F to 86°F). Brief exposure to temperatures up to 40°C (104°F) may be tolerated provided the mean kinetic temperature does not exceed 25°C (77°F); however, such exposure should be minimized. Protect from freezing and excessive heat. Keep bottle tightly closed.

Distributed By:
Sterling-Knight Pharmaceuticals, LLC
Ripley, MS 38663

Item: 810 Rev. 09/19